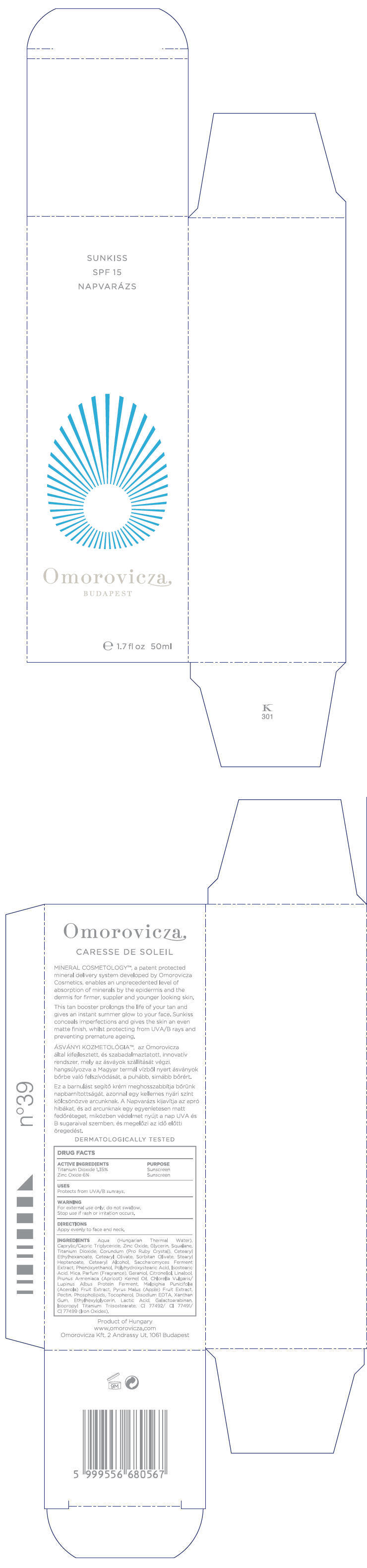 DRUG LABEL: Sunkiss 
NDC: 41442-133 | Form: CREAM
Manufacturer: Omorovicza Kozmetikai Kft
Category: otc | Type: HUMAN OTC DRUG LABEL
Date: 20110506

ACTIVE INGREDIENTS: titanium dioxide 0.675 mL/50 mL; zinc oxide 3 mL/50 mL
INACTIVE INGREDIENTS: CAPRYLIC/CAPRIC MONO/DIGLYCERIDES; glycerin; squalane; aluminum oxide; sorbitan olivate; STEARYL ETHYLHEXANOATE; cetostearyl alcohol; PHENOXYETHANOL; HYDROXYSTEARIC ACID; isostearic acid; mica; geraniol; .BETA.-CITRONELLOL, (R)-; linalool, dl-; APRICOT KERNEL OIL; acerola; apple; pectin; alpha-tocopherol; Edetate Disodium; xanthan gum; ethylhexylglycerin; lactic acid; ferric oxide red; ferric oxide yellow; ferrosoferric oxide

SUNKISS
SPF 15
NAPVARÁZS

Drug Facts

ACTIVE INGREDIENT

ACTIVE INGREDIENTS | PURPOSE
Titanium Dioxide 1.35% | Sunscreen
Zinc Oxide 6% | Sunscreen

USES

Protects from UVA/B sunrays.

WARNING

For external use only; do not swallow.

Stop use if rash or irritation occurs.

DIRECTIONS

Appy evenly to face and neck.

INGREDIENTS

Aqua (Hungarian Thermal Water), Caprylic/Capric Triglyceride, Zinc Oxide, Glycerin, Squalane, Titanium Dioxide, Corundum (Pro Ruby Crystal), Cetearyl Ethylhexanoate, Cetearyl Olivate, Sorbitan Olivate, Stearyl Heptanoate, Cetearyl Alcohol, Saccharomyces Ferment Extract, Phenoxyethanol, Polyhydroxystearic Acid, Isostearic Acid, Mica, Parfum (Fragrance), Geraniol, Citronellol, Linalool, Prunus Armeniaca (Apricot) Kernel Oil, Chlorella Vulgaris/Lupinus Albus Protein Ferment, Malpighia Punicifolia (Acerola) Fruit Extract, Pyrus Malus (Apple) Fruit Extract, Pectin, Phospholipids, Tocopherol, Disodium EDTA, Xanthan Gum, Ethylhexylglycerin, Lactic Acid, Galactoarabinan, Isopropyl Titanium Triisostearate, CI 77492/ CI 77491/ CI 77499 (Iron Oxides).

Product of Hungary
www.omorovicza.com
Omorovicza Kft, 2 Andrassy Ut, 1061 Budapest

PRINCIPAL DISPLAY PANEL - 50ml Bottle Carton

SUNKISS
SPF 15
NAPVARÁZS

Omorovicza
BUDAPEST

e 1.7 fl oz 50ml